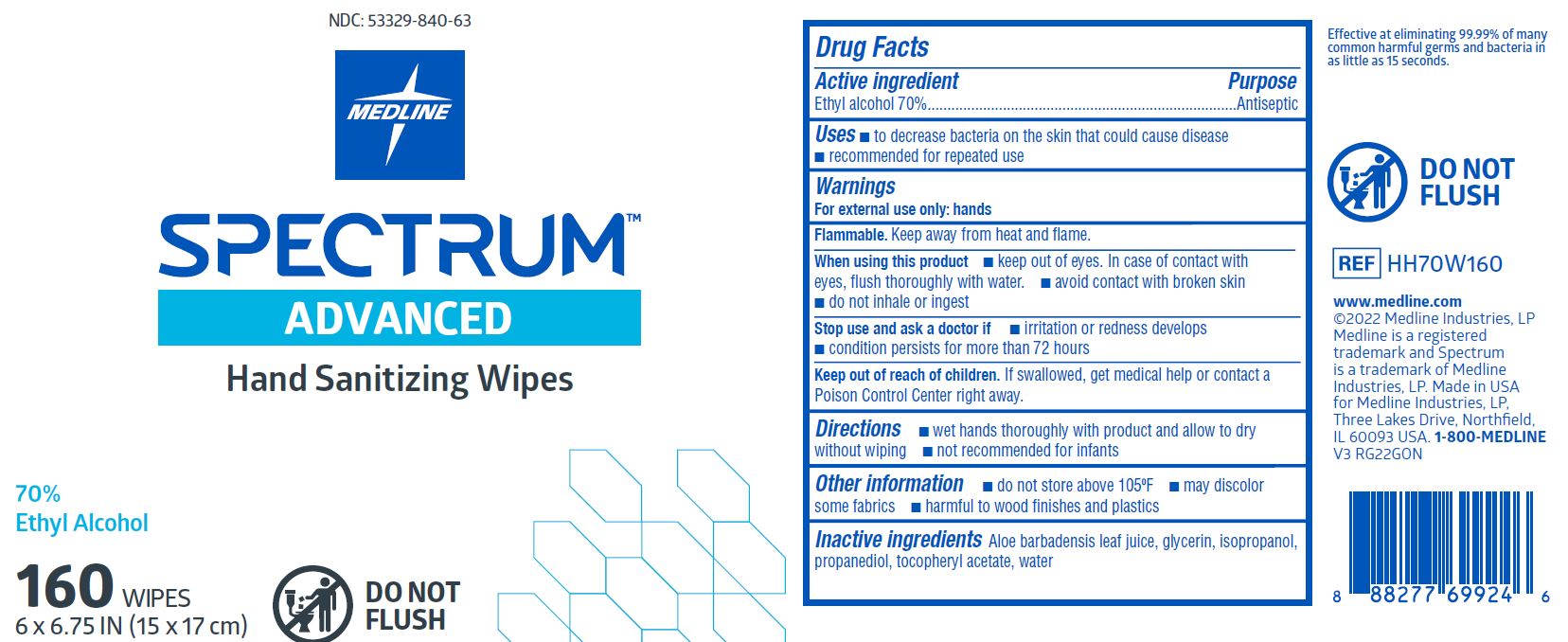 DRUG LABEL: Spectrum Hand Sanitizer Wipes
NDC: 53329-840 | Form: CLOTH
Manufacturer: Medline Industries, LP
Category: otc | Type: HUMAN OTC DRUG LABEL
Date: 20251216

ACTIVE INGREDIENTS: ALCOHOL 70 mL/100 mL
INACTIVE INGREDIENTS: .ALPHA.-TOCOPHEROL ACETATE, D-; ALOE VERA LEAF; ISOPROPYL ALCOHOL; GLYCERIN; WATER; PROPANEDIOL

840 Spectrum Hand Sanitizer Wipes

Active ingredient

Ethyl alcohol 70%

Purpose

Antiseptic

Uses

- to decrease bacteria on the skin that could cause disease

Warnings

For external use only: hands

Flammable. Keep away from fire and flame.

When using this product

- keep out of eyes. In case of contact with eyes, flush thoroughly with water.
- avoid contact with broken skin
- do not inhale or ingest

Stop Use and ask a doctor if

- irritation or redness develops
- condition persists for more than 72 hours

Keep out of reach of children.

If swallowed, get medical help or contact a Poison Control Center right away.

Directions

- wet hands thoroughly with product and allow to dry without wiping
- not recommended for infants

Other information

- do not store above 105ºF
- may discolor some fabrics
- harmful to wood finishes and plastics

Inactive ingredients

aloe barbadensis leaf juice, glycerin, isopropanol, propanediol, tocopheryl acetate, water

Manufacturing Information

Manufactured for:

Medline Industries, LP

Three Lakes Drive, Northfield, IL 60093 USA

Made in USA

www.medline.com

1-800-MEDLINE (633-5463)

REF: HH70W160

V3 RG22GON